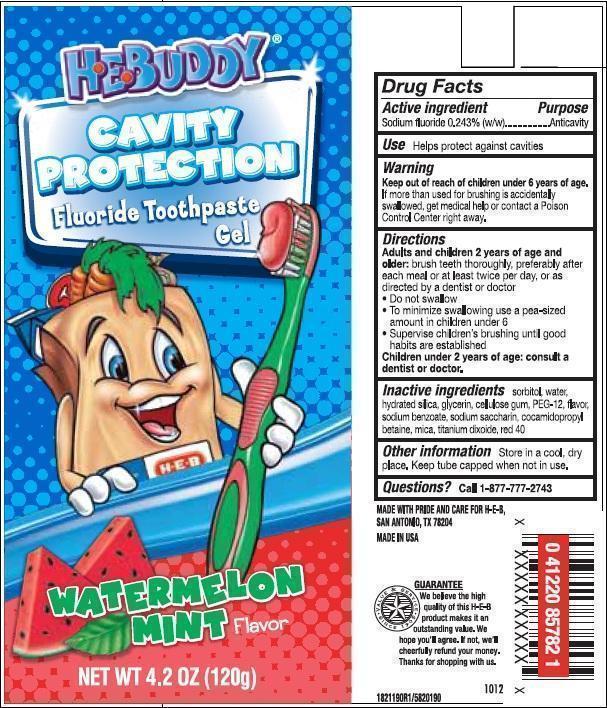 DRUG LABEL: HEB
NDC: 37808-192 | Form: PASTE, DENTIFRICE
Manufacturer: HEB
Category: otc | Type: HUMAN OTC DRUG LABEL
Date: 20251113

ACTIVE INGREDIENTS: SODIUM FLUORIDE 0.15 g/100 g
INACTIVE INGREDIENTS: MICA; GLYCERIN; WATER; SODIUM BENZOATE; SORBITOL; TITANIUM DIOXIDE; SACCHARIN SODIUM; COCAMIDOPROPYL BETAINE; HYDRATED SILICA; POLYETHYLENE GLYCOL 600; CARBOXYMETHYLCELLULOSE SODIUM, UNSPECIFIED FORM; FD&C RED NO. 40

5820034 HEB Cavity Protection Watermelon Mint (8015188)

Drug Facts

Active ingredient

Sodium Fluoride 0.243%

Purpose

Anticavity

INDICATIONS AND USAGE

UseHelps protect against cavities

Warnings

Keep out of reach of children under 6 years of age.If more than used for brushing is accidentally swallowed, get medical help or contact a Poison Control Center right away.

Directions

Adults and children 2 years of age and older:brush teeth thoroughly preferably after each meal or at least twice a day, or as directed by a dentist or doctor.

- Do not swallow
- To minimize swallowing use a pea-sized amount in children under 6
- Supervise childrens brushing until good habits are established

Children under 2 years of age: consult a dentist or doctor.

Other information

Store in a cool dry place. Keep tube capped when not in use.

INACTIVE INGREDIENT

Inactive ingredientssorbitol, water, hydrated silica, glycerin, cellulose gum, PEG-12, flavor, sodium benzoate, sodium saccharin, cocamidopropyl betaine, mica, titanium dioxide, red 40

Questions?Call 1-877-777-2743

MADE WITH PRIDE AND CARE FOR H-E-B,

SAN ANTONIO, TX 78204

MADE IN USA